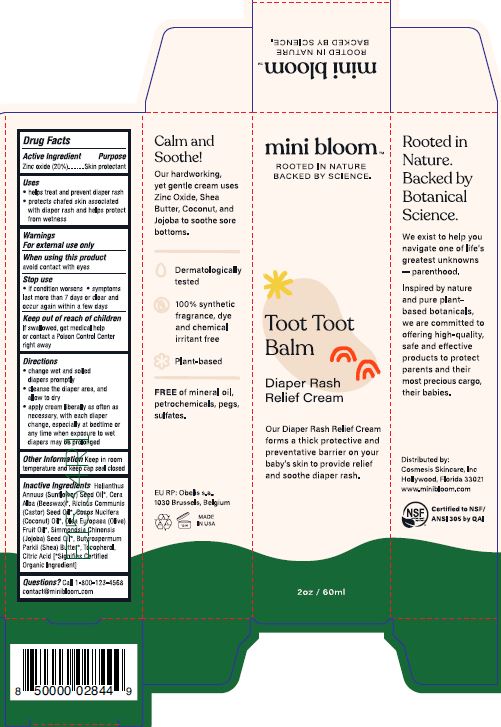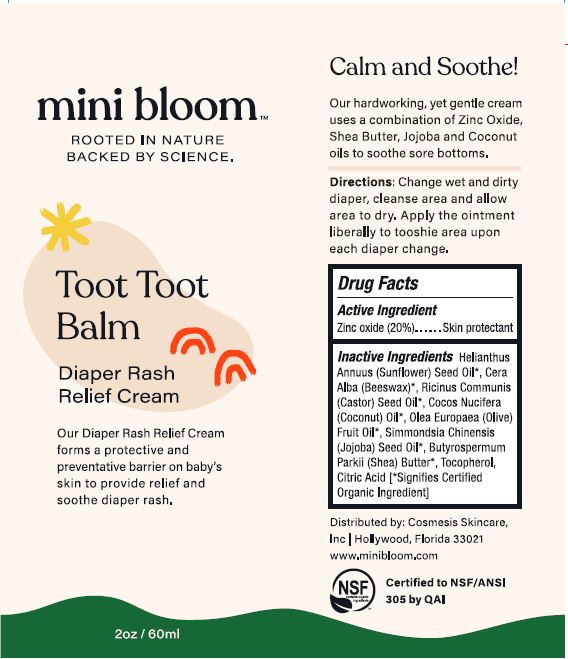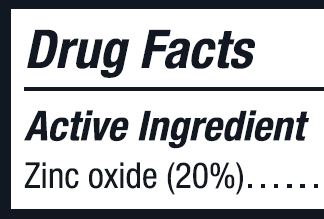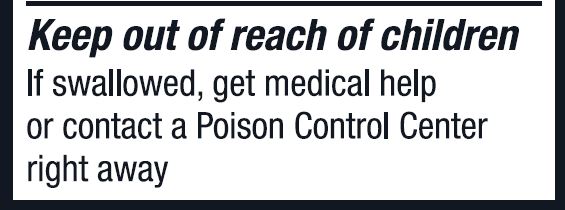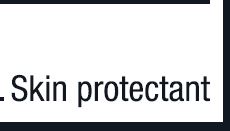 DRUG LABEL: Diaper Cream
NDC: 62932-235 | Form: OINTMENT
Manufacturer: Private Label Select Ltd CO
Category: otc | Type: HUMAN OTC DRUG LABEL
Date: 20201230

ACTIVE INGREDIENTS: ZINC OXIDE 20 g/100 g
INACTIVE INGREDIENTS: WHITE WAX; JOJOBA OIL; SUNFLOWER OIL; .ALPHA.-TOCOPHEROL, D-; SHEA BUTTER; .GAMMA.-TOCOPHEROL; .BETA.-TOCOPHEROL; .DELTA.-TOCOPHEROL; CASTOR OIL; COCONUT OIL; OLIVE OIL

Mini Bloom (Goldfaden) Toot Toot Balm